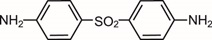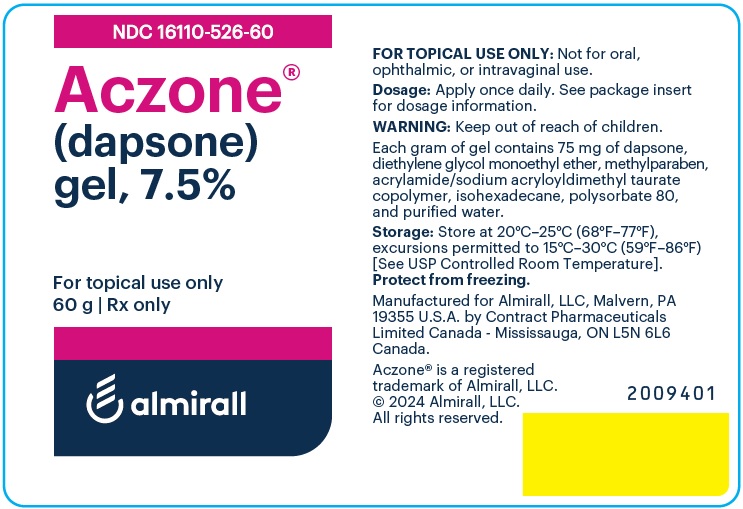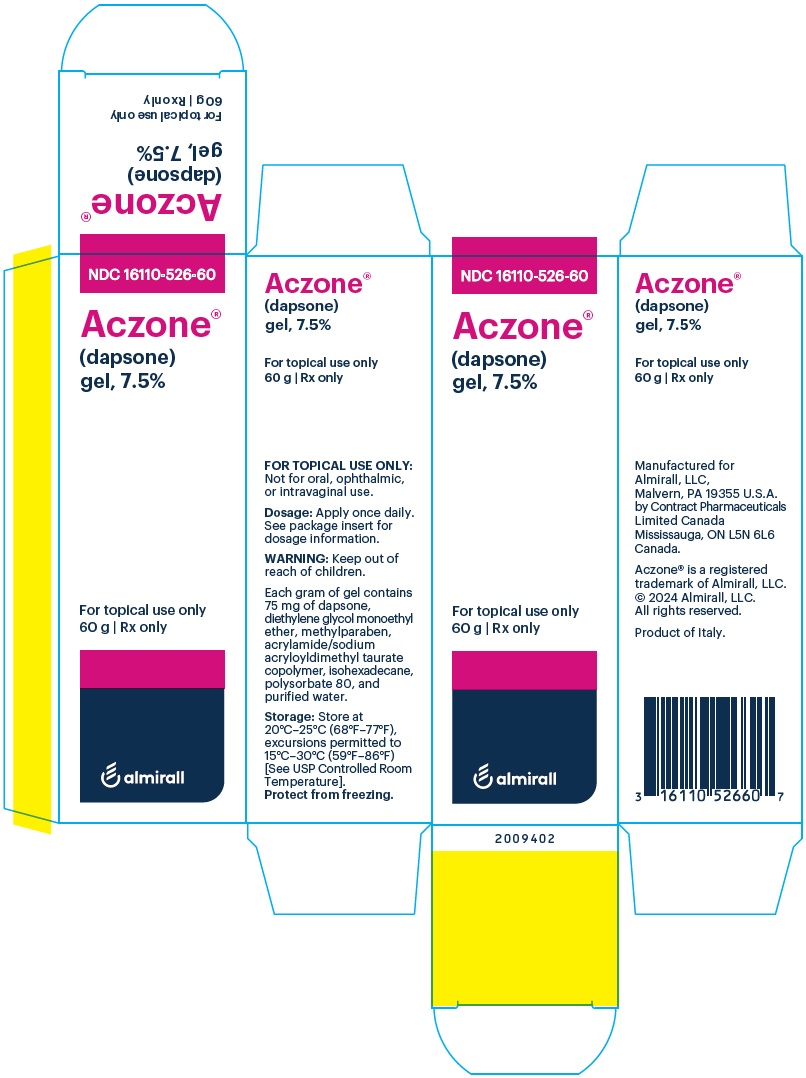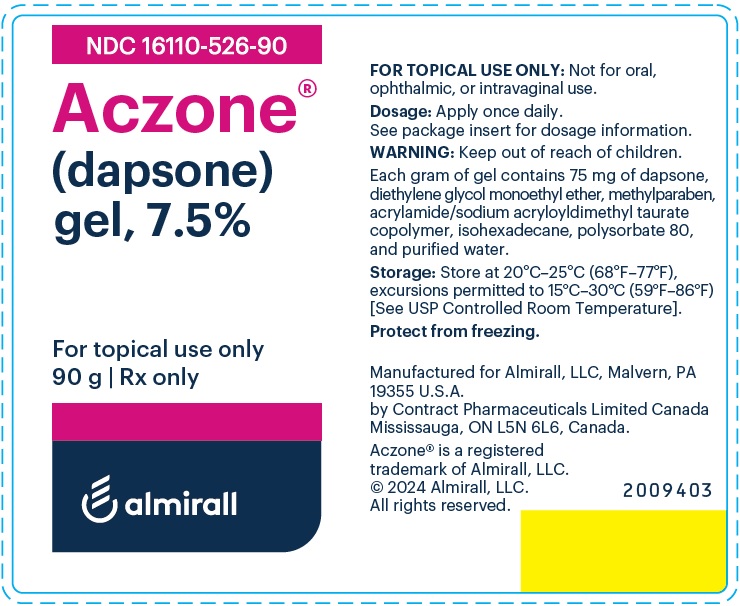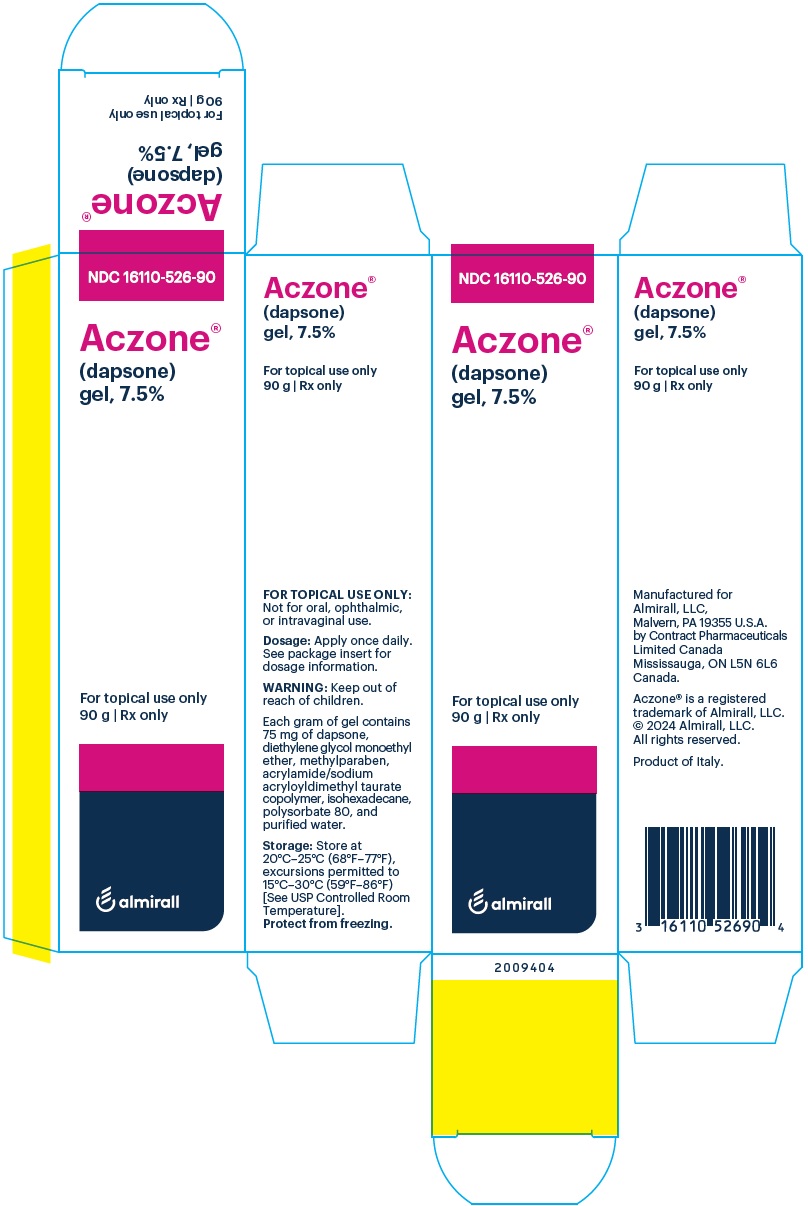 DRUG LABEL: Aczone
NDC: 16110-526 | Form: GEL
Manufacturer: Almirall, LLC
Category: prescription | Type: HUMAN PRESCRIPTION DRUG LABEL
Date: 20251023

ACTIVE INGREDIENTS: DAPSONE 75 mg/1 g
INACTIVE INGREDIENTS: DIETHYLENE GLYCOL MONOETHYL ETHER; METHYLPARABEN; SODIUM ACRYLOYLDIMETHYLTAURATE-ACRYLAMIDE COPOLYMER (1:1; 90000-150000 MPA.S); ISOHEXADECANE; POLYSORBATE 80; WATER

HIGHLIGHTS OF PRESCRIBING INFORMATION

These highlights do not include all the information needed to use ACZONE® Gel, 7.5% safely and effectively. See full prescribing information for ACZONE® Gel, 7.5%.
ACZONE® (dapsone) Gel, 7.5%, for topical use
Initial U.S. Approval: 1955

RECENT MAJOR CHANGES

Indications and Usage (1) | 09/2019

1 INDICATIONS AND USAGE

ACZONE® Gel, 7.5%, is a sulfone indicated for the topical treatment of acne vulgaris in patients 9 years of age and older (1).

2 DOSAGE AND ADMINISTRATION

- Apply once daily (2).
- Apply approximately a pea-sized amount of ACZONE Gel, 7.5%, in a thin layer to the entire face. A thin layer can also be applied to other affected areas (2).
- If there is no improvement after 12 weeks, treatment with ACZONE Gel, 7.5% should be reassessed (2).
- For topical use only. Not for oral, ophthalmic, or intravaginal use (2).

3 DOSAGE FORMS AND STRENGTHS

Gel, 7.5% (3).

4 CONTRAINDICATIONS

None (4).

5 WARNINGS AND PRECAUTIONS

- Methemoglobinemia: Cases of methemoglobinemia have been reported. Discontinue ACZONE Gel if signs of methemoglobinemia occur (5.1).
- Hemolysis: Some patients with Glucose-6-phosphate Dehydrogenase (G6PD) deficiency using topical dapsone developed laboratory changes suggestive of hemolysis (5.1)(8.6).

6 ADVERSE REACTIONS

Most common (incidence ≥ 0.9%) adverse reactions are application site dryness and pruritus (6.1).

To report SUSPECTED ADVERSE REACTIONS, contact Almirall at 1-866-665-2782 or FDA at 1-800-FDA-1088 or www.fda.gov/medwatch.

7 DRUG INTERACTIONS

- Trimethoprim/sulfamethoxazole (TMP/SMX) increases the systemic level of dapsone and its metabolites (7.1).
- Topical benzoyl peroxide used at the same time as ACZONE Gel, 7.5% may result in temporary local yellow or orange skin discoloration (7.2).

FULL PRESCRIBING INFORMATION

1 INDICATIONS AND USAGE

ACZONE® (dapsone) Gel, 7.5%, is indicated for the topical treatment of acne vulgaris in patients 9 years of age and older.

2 DOSAGE AND ADMINISTRATION

For topical use only. Not for oral, ophthalmic, or intravaginal use.

After the skin is gently washed and patted dry, apply approximately a pea-sized amount of ACZONE Gel, 7.5%, in a thin layer to the entire face once daily. In addition, a thin layer may be applied to other affected areas once daily. Rub in ACZONE Gel, 7.5%, gently and completely.

If there is no improvement after 12 weeks, treatment with ACZONE Gel, 7.5% should be reassessed.

3 DOSAGE FORMS AND STRENGTHS

Gel, 7.5%. Each gram of ACZONE Gel, 7.5% contains 75 mg of dapsone in an off-white to yellow gel with suspended particles.

4 CONTRAINDICATIONS

None.

5 WARNINGS AND PRECAUTIONS

5.1 Hematological Effects

Methemoglobinemia

Cases of methemoglobinemia, with resultant hospitalization, have been reported postmarketing in association with twice daily dapsone gel, 5%, treatment. Patients with glucose-6-phosphate dehydrogenase deficiency or congenital or idiopathic methemoglobinemia are more susceptible to drug-induced methemoglobinemia. Avoid use of ACZONE Gel, 7.5% in those patients with congenital or idiopathic methemoglobinemia.

Signs and symptoms of methemoglobinemia may be delayed some hours after exposure. Initial signs and symptoms of methemoglobinemia are characterized by a slate grey cyanosis seen in e.g., buccal mucous membranes, lips, and nail beds. Advise patients to discontinue ACZONE Gel, 7.5% and seek immediate medical attention in the event of cyanosis.

Dapsone can cause elevated methemoglobin levels particularly in conjunction with methemoglobin-inducing agents [see Drug Interactions (7.4)].

Hemolysis

Oral dapsone treatment has produced dose-related hemolysis and hemolytic anemia. Individuals with glucose-6-phosphate dehydrogenase (G6PD) deficiency are more prone to hemolysis with the use of certain drugs. G6PD deficiency is most prevalent in populations of African, South Asian, Middle Eastern, and Mediterranean ancestry.

In clinical trials, there was no evidence of clinically relevant hemolysis or hemolytic anemia in subjects treated with topical dapsone. Some subjects with G6PD deficiency using dapsone gel, 5 %, twice daily developed laboratory changes suggestive of hemolysis [see Use in Specific Populations (8.6)].

Discontinue ACZONE Gel, 7.5%, if signs and symptoms suggestive of hemolytic anemia occur. Avoid use of ACZONE Gel, 7.5% in patients who are taking oral dapsone or antimalarial medications because of the potential for hemolytic reactions. Combination of ACZONE Gel, 7.5%, with trimethoprim/sulfamethoxazole (TMP/SMX) may increase the likelihood of hemolysis in patients with G6PD deficiency [see Drug Interactions (7.1)].

5.2 Peripheral Neuropathy

Peripheral neuropathy (motor loss and muscle weakness) has been reported with oral dapsone treatment. No events of peripheral neuropathy were observed in clinical trials with topical dapsone treatment.

5.3 Skin Reactions

Skin reactions (toxic epidermal necrolysis, erythema multiforme, morbilliform and scarlatiniform reactions, bullous and exfoliative dermatitis, erythema nodosum, and urticaria) have been reported with oral dapsone treatment. These types of skin reactions were not observed in clinical trials with topical dapsone treatment.

6 ADVERSE REACTIONS

6.1 Clinical Studies Experience

Because clinical trials are conducted under widely varying conditions, adverse reaction rates observed in the clinical trials of a drug cannot be directly compared to rates in the clinical trials of another drug and may not reflect the rates observed in practice.

A total of 2161 subjects were treated with ACZONE Gel, 7.5%, for 12 weeks in 2 controlled clinical trials. The population ranged in age from 12 to 63 years, was 56% female, and 58% Caucasian. Adverse drug reactions that were reported in at least 0.9% of subjects treated with ACZONE Gel, 7.5% appear in Table 1 below.

Table 1. Adverse Reactions Occurring in at Least 0.9% of Subjects with Acne Vulgaris in 12-week Controlled Clinical Trials
 | ACZONE Gel, 7.5% (N=2161) | Vehicle (N=2175)
Application Site Dryness | 24 (1.1%) | 21 (1.0%)
Application Site Pruritus | 20 (0.9%) | 11 (0.5%)

6.2 Experience with Oral Use of Dapsone

Although not observed in the clinical trials with topical dapsone, serious adverse reactions have been reported with oral use of dapsone, including agranulocytosis, hemolytic anemia, peripheral neuropathy (motor loss and muscle weakness), and skin reactions (toxic epidermal necrolysis, erythema multiforme, morbilliform and scarlatiniform reactions, bullous and exfoliative dermatitis, erythema nodosum, and urticaria).

6.3 Postmarketing Experience

Because these reactions are reported voluntarily from a population of uncertain size, it is not always possible to reliably estimate their frequency or establish a causal relationship to drug exposure.

The following adverse reactions have been identified during post-approval use of topical dapsone: methemoglobinemia, rash (including erythematous rash, application site rash) and swelling of face (including lip swelling, eye swelling).

7 DRUG INTERACTIONS

No formal drug-drug interaction studies were conducted with ACZONE Gel, 7.5%.

7.1 Trimethoprim-Sulfamethoxazole

A drug-drug interaction study evaluated the effect of the use of dapsone gel, 5% in combination with double strength (160 mg/800 mg) trimethoprim-sulfamethoxazole (TMP/SMX). During co-administration, systemic levels of TMP and SMX were essentially unchanged, however, levels of dapsone and its metabolites increased in the presence of TMP/SMX. The systemic exposure from ACZONE Gel, 7.5% is expected to be about 1% of that from the 100 mg oral dose, even when co-administered with TMP/SMX.

7.2 Topical Benzoyl Peroxide

Topical application of dapsone gel followed by benzoyl peroxide in patients with acne vulgaris may result in a temporary local yellow or orange discoloration of the skin and facial hair.

7.3 Drug Interactions with Oral Dapsone

Certain concomitant medications (such as rifampin, anticonvulsants, St. John’s wort) may increase the formation of dapsone hydroxylamine, a metabolite of dapsone associated with hemolysis. With oral dapsone treatment, folic acid antagonists such as pyrimethamine have been noted to possibly increase the likelihood of hematologic reactions.

7.4 Concomitant Use with Drugs that Induce Methemoglobinemia

Concomitant use of ACZONE Gel, 7.5% with drugs that induce methemoglobinemia such as sulfonamides, acetaminophen, acetanilide, aniline dyes, benzocaine, chloroquine, dapsone, naphthalene, nitrates and nitrites, nitrofurantoin, nitroglycerin, nitroprusside, pamaquine, para‐aminosalicylic acid, phenacetin, phenobarbital, phenytoin, primaquine, and quinine may increase the risk for developing methemoglobinemia [see Warnings and Precautions (5.1)].

8 USE IN SPECIFIC POPULATIONS

8.1 Pregnancy

Risk Summary

There are no available data on ACZONE Gel, 7.5%, use in pregnant women to inform a drug-associated risk for adverse developmental outcomes. The systemic absorption of ACZONE in humans following topical application is low relative to oral dapsone administration [see Clinical Pharmacology (12.3)]. In animal reproduction studies, oral doses of dapsone administered to pregnant rats and rabbits during organogenesis that resulted in systemic exposures more than 400 times the systemic exposure at the maximum recommended human dose (MRHD) of ACZONE Gel, 7.5%, resulted in embryocidal effects. When orally administered to rats from the onset of organogenesis through the end of lactation at systemic exposures approximately 500 times the exposure at the MRHD, dapsone resulted in increased stillbirths and decreased pup weight [see Data].

The estimated background risks of major birth defects and miscarriage for the indicated population are unknown. In the U.S. general population, the estimated background risk of major birth defects and miscarriage in clinically recognized pregnancies is 2-4% and 15-20%, respectively.

Data

Animal Data

Dapsone has been shown to have an embryocidal effect in rats and rabbits when administered orally daily to females during organogenesis at dosages of 75 mg/kg/day and 150 mg/kg/day, respectively. These dosages resulted in systemic exposures that represented approximately 1407 times [rats] and 425 times [rabbits] the systemic exposure observed in human females as a result of use of the MRHD of ACZONE Gel, 7.5%, based on AUC comparisons. These effects were probably secondary to maternal toxicity.

Dapsone was assessed for effects on perinatal/postnatal pup development and postnatal maternal behavior and function in a study in which dapsone was orally administered to female rats daily beginning on the seventh day of gestation and continuing until the twenty-seventh day postpartum. Maternal toxicity (decreased body weight and food consumption) and developmental effects (increase in stillborn pups and decreased pup weight) were seen at a dapsone dose of 30 mg/kg/day (approximately 563 times the systemic exposure that is associated with the MRHD of ACZONE Gel, 7.5%, based on AUC comparisons). No effects were observed on the viability, physical development, behavior, learning ability, or reproductive function of surviving pups.

8.2 Lactation

Risk Summary

There is no information regarding the presence of topical dapsone in breastmilk, the effects on the breastfed infant or the effects on milk production. Orally administered dapsone appears in human milk and could result in hemolytic anemia and hyperbilirubinemia especially in infants with G6PD deficiency. Systemic absorption of dapsone following topical application is low relative to oral dapsone administration.

The developmental and health benefits of breastfeeding should be considered along with the mother’s clinical need for ACZONE Gel, 7.5% and any potential adverse effects on the breastfed child from ACZONE Gel, 7.5% or from the underlying maternal condition.

8.4 Pediatric Use

The safety and effectiveness of ACZONE Gel, 7.5% for the topical treatment of acne vulgaris have been established in patients 9 years of age and older. Use of ACZONE Gel, 7.5% in patients 9 to 11 years of age for this indication is supported by evidence from adequate and well-controlled clinical trials in 1066 subjects 12 years of age and older and with additional pharmacokinetic and safety data in pediatric subjects 9 to 11 years of age from an open label study of 100 subjects with acne [see Adverse Reactions (6.1), and Clinical Pharmacology (12.3)].

The safety profile for ACZONE Gel, 7.5% in clinical trials was similar to the vehicle control group.

Safety and effectiveness of ACZONE Gel, 7.5%, have not been established in pediatric patients below the age of 9 years.

8.5 Geriatric Use

Clinical trials of ACZONE Gel, 7.5% did not include sufficient numbers of subjects aged 65 years and over to determine whether they respond differently from younger subjects.

8.6 Glucose-6-phosphate Dehydrogenase (G6PD) Deficiency

Individuals with glucose-6-phosphate dehydrogenase (G6PD) deficiency may be more prone to methemoglobinemia and hemolysis [see Warnings and Precautions (5.1)].

ACZONE Gel, 5% and vehicle were evaluated in a randomized, double-blind, cross-over design clinical study of 64 subjects with G6PD deficiency and acne vulgaris. Subjects were Black (88%), Asian (6%), Hispanic (2%) or of other racial origin (5%). Blood samples were taken at Baseline, Week 2, and Week 12 during both vehicle and ACZONE Gel, 5% treatment periods. Some of these subjects developed laboratory changes suggestive of hemolysis, but there was no evidence of clinically significant hemolytic anemia in this study [see Warnings and Precautions (5.1)].

11 DESCRIPTION

ACZONE (dapsone) Gel, 7.5%, contains dapsone, a sulfone, in an aqueous gel base for topical dermatologic use. ACZONE Gel, 7.5% is an off-white to yellow gel with suspended particles. Chemically, dapsone has an empirical formula of C12H12N2O2S. It is a white or slightly yellow-white, crystalline powder that has a molecular weight of 248.30. Dapsone’s chemical name is 4-[(4-aminobenzene) sulfonyl] aniline and its structural formula is:

Each gram of ACZONE Gel, 7.5%, contains 75 mg of dapsone, USP, in a gel of diethylene glycol monoethyl ether, methylparaben, acrylamide/sodium acryloyldimethyl taurate copolymer, isohexadecane, polysorbate 80, and purified water.

12 CLINICAL PHARMACOLOGY

12.1 Mechanism of Action

The mechanism of action of dapsone gel in treating acne vulgaris is not known.

12.3 Pharmacokinetics

In a pharmacokinetic study, male and female subjects 16 years of age or older with acne vulgaris (N=19) applied 2 grams of ACZONE Gel, 7.5% to the face, upper chest, upper back and shoulders once daily for 28 days. Steady state for dapsone was reached within 7 days of dosing. On Day 28, the mean dapsone maximum plasma concentration (Cmax) and area under the concentration-time curve from 0 to 24 hours post dose (AUC0-24h) were 13.0 ± 6.8 ng/mL and 282 ± 146 ng·h/mL, respectively. The systemic exposure from ACZONE Gel, 7.5% is expected to be about 1% of that from a 100 mg oral dose.

Long-term safety studies were not conducted with ACZONE Gel, 7.5%, however, in a long-term clinical study of dapsone gel, 5% treatment (twice daily), periodic blood samples were collected up to 12 months to determine systemic exposure of dapsone and its metabolites in approximately 500 subjects. Based on the measurable dapsone concentrations from 408 subjects (M=192, F=216), obtained at Month 3, neither gender nor race appeared to affect the pharmacokinetics of dapsone. Similarly, dapsone exposures were approximately the same between the age groups of 12-15 years (N=155) and those greater than or equal to 16 years (N=253). There was no evidence of increasing systemic exposure to dapsone over the study year in these subjects.

In an open label safety and pharmacokinetic study in pediatric subjects 9 to 11 years of age with acne vulgaris, a subset of subjects (N = 16) received once daily topical application of approximately 2 grams of ACZONE Gel, 7.5%, to the entire face, shoulders, upper chest and upper back for 8 days. On Day 8, the systemic concentrations were at or near steady state and the mean ± SD systemic concentration of dapsone at 10 hours post dose was 20 ± 12.5 ng/mL.

12.4 Microbiology

In Vivo Activity: No microbiology or immunology studies were conducted during ACZONE Gel, 7.5% clinical studies.

Drug Resistance: No dapsone resistance studies were conducted during dapsone gel clinical studies therefore there are no data available as to whether dapsone treatment may have resulted in decreased susceptibility of Propionibacterium acnes, an organism associated with acne, or to other antimicrobials that may be used to treat acne. Therapeutic resistance to dapsone has been reported for Mycobacterium leprae, when patients have been treated with oral dapsone.

13 NONCLINICAL TOXICOLOGY

13.1 Carcinogenesis, Mutagenesis, Impairment of Fertility

Dapsone was not carcinogenic to rats when orally administered to females for 92 weeks or males for 100 weeks at dose levels up to 15 mg/kg/day (approximately 340 times the systemic exposure observed in humans as a result of use of the MRHD of ACZONE Gel, 7.5%, based on AUC comparisons).

No evidence of potential to induce carcinogenicity was observed in a dermal study in which dapsone gel was topically applied to Tg.AC transgenic mice for approximately 26 weeks. Dapsone concentrations of 3%, 5%, and 10% were evaluated; 3% material was judged to be the maximum tolerated dosage.

Dapsone was negative in a bacterial reverse mutation assay (Ames test), and was negative in a micronucleus assay conducted in mice. Dapsone was positive (clastogenic) in a chromosome aberration assay conducted with Chinese hamster ovary (CHO) cells.

The effects of dapsone on fertility and general reproductive performance were assessed in male and female rats following oral dosing. Dapsone reduced sperm motility at dosages of 3 mg/kg/day or greater (approximately 22 times the systemic exposure that is associated with the MRHD of ACZONE Gel, 7.5%, based on AUC comparisons) when administered daily beginning 63 days prior to mating and continuing through the mating period. The mean numbers of embryo implantations and viable embryos were significantly reduced in untreated females mated with males that had been dosed at 12 mg/kg/day or greater (approximately 187 times the systemic exposure that is associated with the MRHD of ACZONE Gel, 7.5%, based on AUC comparisons), presumably due to reduced numbers or effectiveness of sperm, indicating impairment of fertility. When administered to female rats at a dosage of 75 mg/kg/day (approximately 1407 times the systemic exposure that is associated with the MRHD of ACZONE Gel, 7.5%, based on AUC comparisons) for 15 days prior to mating and for 17 days thereafter, dapsone reduced the mean number of implantations, increased the mean early resorption rate, and reduced the mean litter size. These effects probably were secondary to maternal toxicity.

14 CLINICAL STUDIES

The safety and efficacy of once daily use of ACZONE Gel, 7.5%, was assessed in two 12-week multicenter, randomized, double-blind, vehicle-controlled trials. Efficacy was assessed in a total of 4340 subjects 12 years of age and older. The majority of the subjects had moderate acne vulgaris, 20 to 50 inflammatory and 30 to 100 non-inflammatory lesions at baseline, and were randomized to receive either ACZONE Gel, 7.5% or vehicle.

Treatment response was defined at Week 12 as the proportion of subjects who were rated “none” or “minimal” with at least a two-grade improvement from baseline on the Global Acne Assessment Score (GAAS), and mean absolute change from baseline in both inflammatory and non-inflammatory lesion counts. A GAAS score of “none” corresponded to no evidence of facial acne vulgaris. A GAAS score of “minimal” corresponded to a few non-inflammatory lesions (comedones) being present and to a few inflammatory lesions (papules/pustules) that may be present.

The GAAS success rate, mean reduction, and percent reduction in acne lesion counts from baseline after 12 weeks of treatment are presented in the following table.

Table 2. Clinical Efficacy of ACZONE® Gel at Week 12 in Subjects with Acne Vulgaris
 | Trial 1 |  | Trial 2
 | ACZONE® Gel, 7.5% (N=1044) | Vehicle (N=1058) | ACZONE® Gel, 7.5% (N=1118) | Vehicle (N=1120)
Global Acne Assessment Score
GAAS Success (Score 0 or 1) | 30% | 21% | 30% | 21%
Inflammatory Lesions
Mean absolute reduction | 16.1 | 14.3 | 15.6 | 14.0
Mean percent reduction | 56% | 49% | 54% | 48%
Non-inflammatory Lesions
Mean absolute reduction | 20.7 | 18.0 | 20.8 | 18.7
Mean percent reduction | 45% | 39% | 46% | 41%

16 HOW SUPPLIED/STORAGE AND HANDLING

ACZONE Gel is an off-white to yellow gel with suspended particles. It is supplied in an airless pump containing a polypropylene bottle with a high density polyethylene piston.

ACZONE (dapsone) Gel, 7.5%, is supplied in the following sizes:

NDC 16110-526-30 30 gram pump

NDC 16110-526-60 60 gram pump

NDC 16110-526-90 90 gram pump

STORAGE AND HANDLING

Storage: Store at 20°C-25°C (68°F-77°F), excursions permitted to 15°C-30°C (59°F-86°F) [see USP Controlled Room Temperature]. Protect from freezing.

17 PATIENT COUNSELING INFORMATION

Advise the patient to read the FDA-approved patient labeling (Patient Information).

Hematological Effects

- Inform patients that methemoglobinemia can occur with topical dapsone treatment. Advise patients to seek immediate medical attention if they develop cyanosis [see Warnings and Precautions (5.1)].
- Inform patients who have G6PD deficiency that hemolytic anemia may occur with topical dapsone treatment. Advise patients to seek medical attention if they develop signs and symptoms suggestive of hemolytic anemia [see Warnings and Precautions (5.1)].

Important Administration Instructions

- Advise patients to apply ACZONE Gel, 7.5%, once daily to the entire face [see Dosage and Administration (2)].
- ACZONE Gel, 7.5% is for topical use only.
- Do not apply ACZONE Gel, 7.5% to eyes, mouth, or mucous membranes.

Distributed by: Almirall, LLC.

Malvern, PA 19355

Aczone® is a registered trademark of Almirall, LLC

© 2019 Almirall, LLC. All rights reserved.
Patented.

Patient Information

ACZONE® (AK-zōn) (dapsone) Gel, 7.5%

Important: For use on skin only (topical use). Do not use ACZONE Gel, 7.5% in your mouth, eyes, or vagina.

What is ACZONE Gel, 7.5%?

ACZONE Gel, 7.5%, is a prescription medicine used on the skin (topical) to treat acne in people 9 years and older.

ACZONE Gel, 7.5%, has not been studied in children under 9 years of age.

Before you use ACZONE Gel, 7.5%, tell your doctor about all of your medical conditions, including if you:

- have a glucose-6-phosphate dehydrogenase deficiency (G6PD)
- have higher than normal levels of methemoglobin in your blood (methemoglobinemia)
- are pregnant or plan to become pregnant. It is not known if ACZONE Gel, 7.5% will harm your unborn baby.
- are breastfeeding or plan to breastfeed. ACZONE Gel, 7.5% can pass into your breast milk and may harm your baby. You and your doctor should decide if you will use ACZONE Gel, 7.5%, or breastfeed. You should not do both.

Tell your doctor about all the medicines you take, including prescription and over-the-counter medicines, vitamins, and herbal supplements. Especially, tell your doctor if you are using acne medicines that contain benzoyl peroxide. Use of benzoyl peroxide with ACZONE Gel, 7.5% at the same time may cause your skin or facial hair to temporarily turn yellow or orange at the site of application.

How do I use ACZONE Gel, 7.5%?

- Use ACZONE Gel, 7.5% exactly as your doctor tells you to use it.
- Apply ACZONE Gel, 7.5% one time a day.
- Gently wash and pat dry the areas of your skin where you will apply ACZONE Gel, 7.5%.
- Apply a pea-sized amount of ACZONE Gel, 7.5% in a thin layer to the entire face. A thin layer may also be applied to other affected areas as instructed by your doctor.
- Rub ACZONE Gel, 7.5% in gently and completely.
- Wash your hands after applying ACZONE Gel, 7.5%.
- If your acne does not get better after using ACZONE Gel, 7.5% for 12 weeks, talk to your doctor about continuing treatment.

What are the possible side effects of ACZONE Gel, 7.5%?

ACZONE Gel, 7.5% may cause serious side effects, including:

- Decrease of oxygen in your blood caused by a certain type of abnormal red blood cell (methemoglobinemia). Stop using ACZONE Gel, 7.5% and get medical help right away if your lips, nail beds, or the inside of your mouth turns grey or blue.
- Breakdown of red blood cells (hemolytic anemia). Some people with G6PD deficiency using ACZONE Gel, 7.5% may develop mild hemolytic anemia. Stop using ACZONE Gel, 7.5% and tell your doctor right away if you get any of the following signs and symptoms:
  - back pain
  - dark brown urine
  - shortness of breath
  - fever
  - tiredness or weakness
  - yellow or pale skin

The most common side effects of ACZONE Gel, 7.5% include dryness and itching of the skin being treated. These are not all of the possible side effects of ACZONE Gel, 7.5%. Call your doctor for medical advice about side effects. You may report side effects to FDA at 1-800-FDA-1088.

How should I store ACZONE Gel, 7.5%?

- Store ACZONE Gel, 7.5%, at room temperature 68°F to 77°F (20°C to 25°C).
- Protect ACZONE Gel, 7.5% from freezing.

Keep ACZONE Gel, 7.5% and all medicines out of the reach of children.

General information about the safe and effective use of ACZONE Gel, 7.5%.

Medicines are sometimes prescribed for purposes other than those listed in a Patient Information leaflet. Do not use ACZONE Gel, 7.5% for a condition for which it was not prescribed. Do not give ACZONE Gel, 7.5% to other people, even if they have the same symptoms you have. It may harm them. You can ask your doctor or pharmacist for information about ACZONE Gel, 7.5% that is written for health professionals.

What are the ingredients in ACZONE Gel, 7.5%?

Active ingredient: dapsone

Inactive ingredients: diethylene glycol monoethyl ether, methylparaben, acrylamide/sodium acryloyldimethyl taurate copolymer, isohexadecane, polysorbate 80, and purified water.

Distributed by: Almirall, LLC

Malvern, PA 19355

Aczone® is a registered trademark of Almirall, LLC

© 2019 Almirall, LLC. All rights reserved.

Patented.

For more information, call 1-866-665-2782

This Patient Information has been approved by the U.S. Food and Drug Administration.

Issued: 12/2021